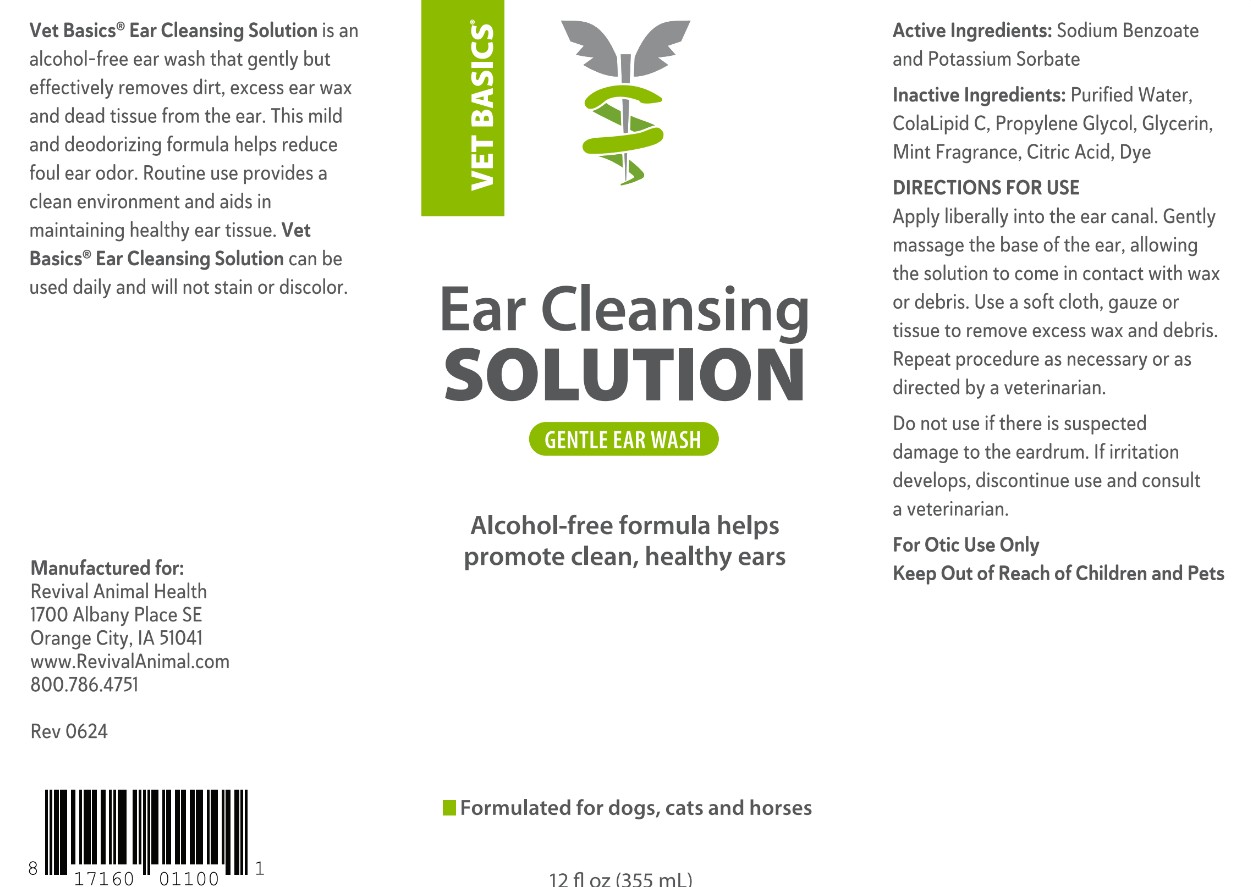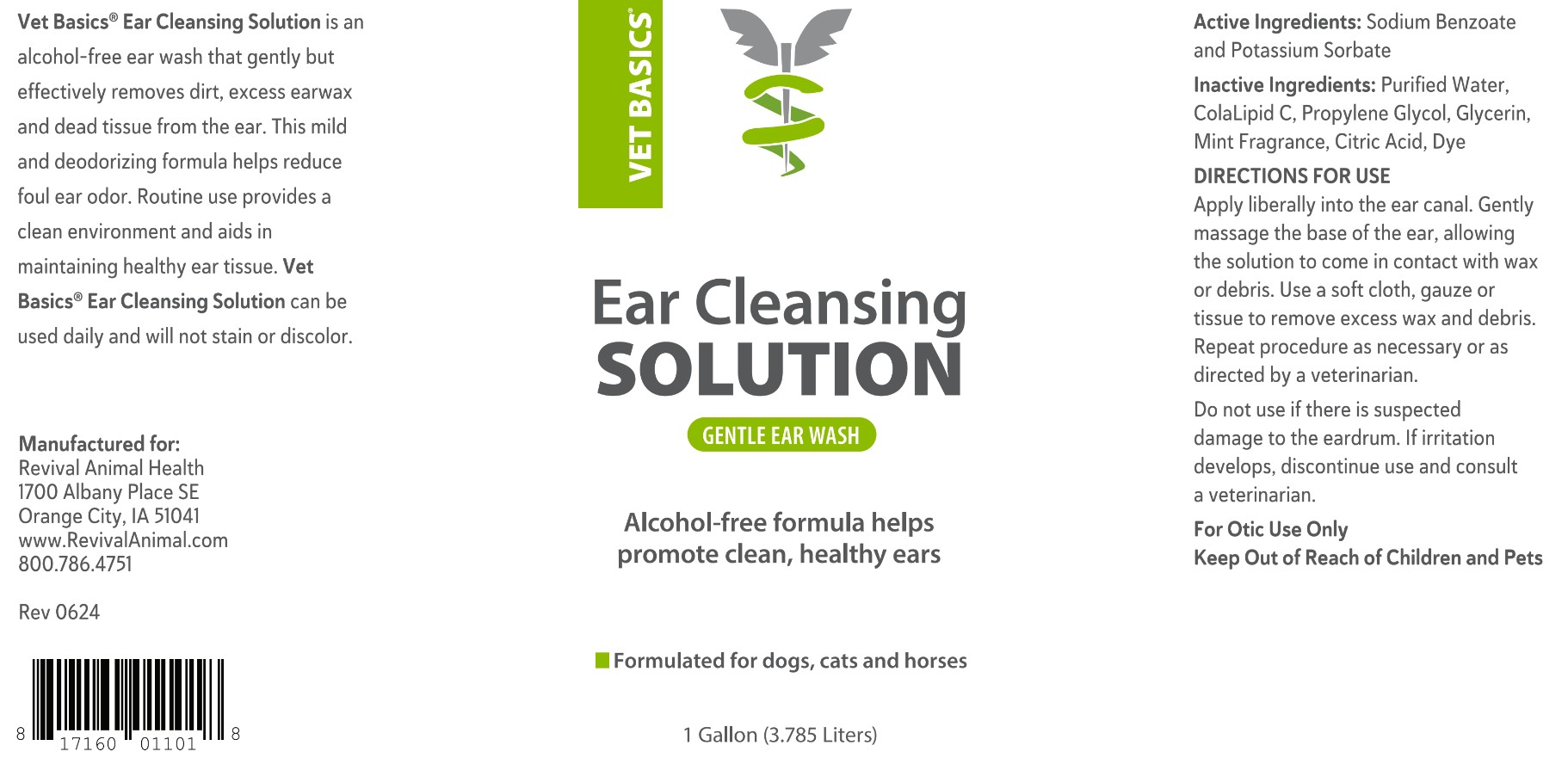 DRUG LABEL: Vet Basics Ear Cleansing Solution
NDC: 86201-0002 | Form: IRRIGANT
Manufacturer: Revival Animal Health
Category: animal | Type: OTC ANIMAL DRUG LABEL
Date: 20241231

ACTIVE INGREDIENTS: potassium sorbate 1.5 mg/1 g; sodium benzoate 3 mg/1 g
INACTIVE INGREDIENTS: COCAMIDOPROPYL PROPYLENE GLYCOL-DIMONIUM CHLORIDE PHOSPHATE; water; propylene glycol; GLYCERIN; FD&C BLUE NO. 1; anhydrous citric acid

INDICATIONS AND USAGE

Vet Basics® Ear Cleansing Solution contains special ingredients to effectively remove dirt, excess earwax and dead tissue from the ear. This mild and deodorizing formula helps to soothe the external ear canal and reduce odor. Routine use provides a clean environment and aids in maintaining healthy ear tissue. Vet Basics® Ear Cleansing Solution can be used daily and will not stain or discolor.

Manufactured for:
Revival Animal Health
1700 Albany Place SE
Orange City, IA 51041
www.RevivalAnimal.com
800.786.4751

Rev 0624

UPC 817160011001 (12 oz)

UPC 817160011018 (1 Gallon)

INACTIVE INGREDIENT

Ingredients: Purified Water, ColaLipid C, Propylene Glycol, Glycerin, Mint Fragrance, Citric Acid, Dye

INDICATIONS AND USAGE

DIRECTIONS FOR USE

Apply liberally into the ear canal. Gently massage the base of the ear, allowing the solution to come in contact with wax or debris. Use a soft cloth, gauze or tissue to remove excess wax and debris. Repeat procedure as necessary or as directed by a veterinarian.

Do not use if there is suspected damage to the eardrum. If irritation develops, discontinue use and consult a veterinarian. For Otic Use Only

Keep Out of Reach of Children and Pets

Active Ingredients: Sodium Benzoate and Potassium Sorbate

PACKAGE LABEL

Vet Basics® Ear Cleansing Solution

Formulated for Routine Cleansing

Regular use helps promote clean, healthy ears

Formulated for dogs, cats and horses

12 fl oz (355 mL)

1 Gallon (3.785 Liters)